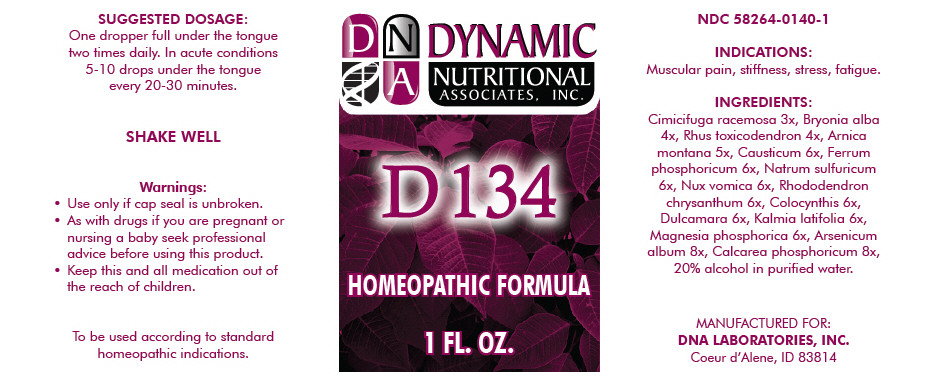 DRUG LABEL: D134
NDC: 58264-0140 | Form: SOLUTION
Manufacturer: DNA Labs, Inc.
Category: homeopathic | Type: HUMAN OTC DRUG LABEL
Date: 20250113

ACTIVE INGREDIENTS: BLACK COHOSH 3 [hp_X]/1 mL; BRYONIA ALBA WHOLE 4 [hp_X]/1 mL; TOXICODENDRON PUBESCENS WHOLE 4 [hp_X]/1 mL; ARNICA MONTANA 5 [hp_X]/1 mL; CAUSTICUM 6 [hp_X]/1 mL; FERROSOFERRIC PHOSPHATE 6 [hp_X]/1 mL; SODIUM SULFATE ANHYDROUS 6 [hp_X]/1 mL; STRYCHNOS NUX-VOMICA SEED 6 [hp_X]/1 mL; RHODODENDRON AUREUM WHOLE 6 [hp_X]/1 mL; CITRULLUS COLOCYNTHIS WHOLE 6 [hp_X]/1 mL; SOLANUM DULCAMARA WHOLE 6 [hp_X]/1 mL; KALMIA LATIFOLIA WHOLE 6 [hp_X]/1 mL; MAGNESIUM PHOSPHATE, DIBASIC TRIHYDRATE 6 [hp_X]/1 mL; ARSENIC TRIOXIDE 8 [hp_X]/1 mL; TRIBASIC CALCIUM PHOSPHATE 8 [hp_X]/1 mL
INACTIVE INGREDIENTS: ALCOHOL; WATER

D134

NDC 58264-0140-1

INDICATIONS

PURPOSE

Muscular pain, stiffness, stress, fatigue.

ACTIVE INGREDIENT

INGREDIENTS

Cimicifuga racemosa 3x, Bryonia alba 4x, Rhus toxicodendron 4x, Arnica montana 5x, Causticum 6x, Ferrum phosphoricum 6x, Natrum sulfuricum 6x, Nux vomica 6x, Rhododendron chrysanthum 6x, Colocynthis 6x, Dulcamara 6x, Kalmia latifolia 6x, Magnesia phosphorica 6x, Arsenicum album 8x, Calcarea phosphoricum 8x, 20% alcohol in purified water.

SUGGESTED DOSAGE

One dropper full under the tongue two times daily. In acute conditions 5-10 drops under the tongue every 20-30 minutes.

STORAGE AND HANDLING

SHAKE WELL

Warnings

- Use only if cap seal is unbroken.

PREGNANCY OR BREAST FEEDING

- As with drugs if you are pregnant or nursing a baby seek professional advice before using this product.

KEEP OUT OF REACH OF CHILDREN

- Keep this and all medication out of the reach of children.

To be used according to standard homeopathic indications.

PRINCIPAL DISPLAY PANEL - 1 FL. OZ. Bottle Label

DYNAMIC
NUTRITIONAL
ASSOCIATES, INC.

D 134

HOMEOPATHIC FORMULA

1 FL. OZ.